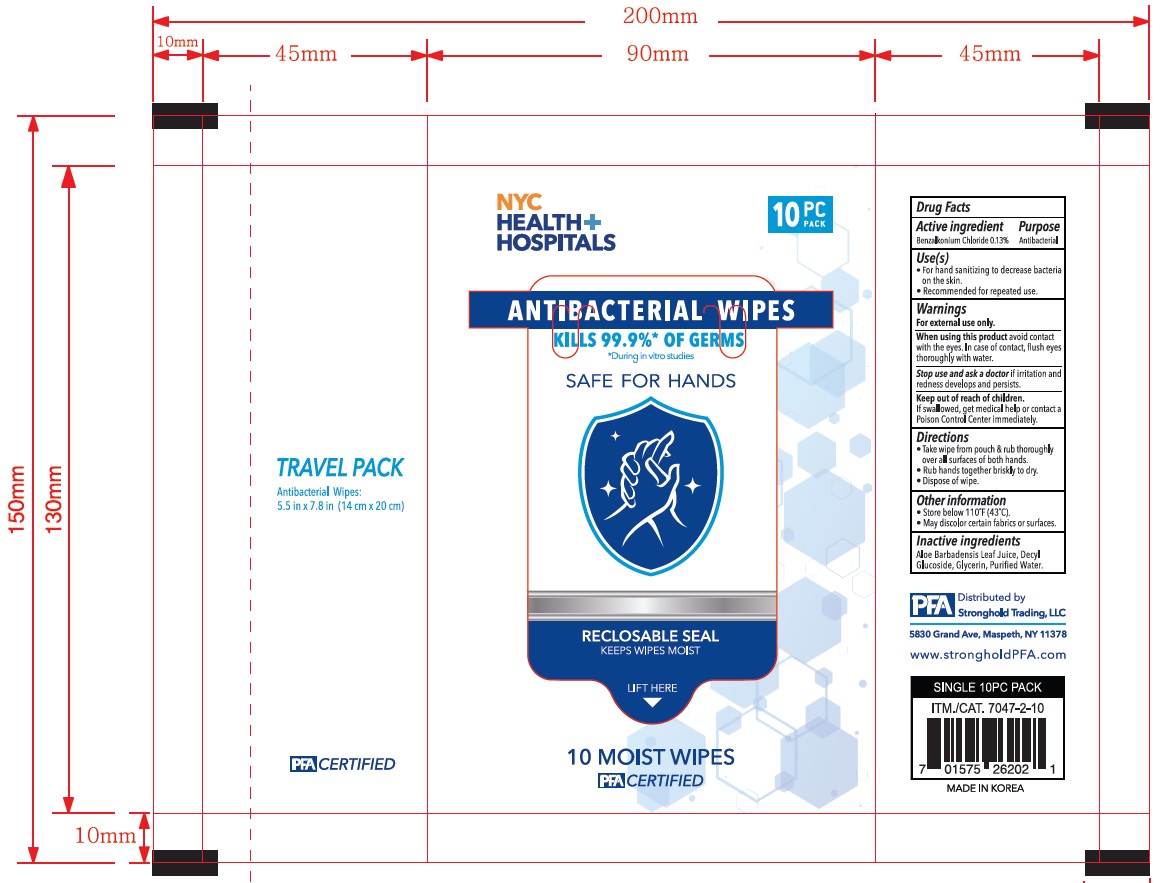 DRUG LABEL: NYCHH ANTIBACTERIAL WIPES
NDC: 81787-010 | Form: CLOTH
Manufacturer: Korea Living Goods Lab
Category: otc | Type: HUMAN OTC DRUG LABEL
Date: 20210408

ACTIVE INGREDIENTS: Benzalkonium chloride 0.0013 1/1 1
INACTIVE INGREDIENTS: Water; ALOE VERA LEAF; Decyl Glucoside; Glycerin

ACTIVE INGREDIENT

Benzalkonium chloride 0.13%

INACTIVE INGREDIENTS

Aloe Barbadensis Leaf Juice, Decyl Glucoside, Glycerin, Purified Water

PURPOSE

Antibacterial

WARNINGS

For external use only.
--------------------------------------------------------------------------------------------------------
When using this product avoid contact with the eyes. In case of contact, flush eyes thoroughly with water
--------------------------------------------------------------------------------------------------------
Stop use and ask a doctor if irritation and redness develops and persists.

KEEP OUT OF REACH OF CHILDREN

If swallowed, get medical help or contact a Poison Control Center immediately.

Use(s)

■ For hand sanitizing to decrease bacteria on the skin.
■ Recommeded for repeated use.

Directions

■ Take wipe from pouch & rub thoroughly over all surfaces of both hands.
■ Rub hands together briskly to dry.
■ Dispose of wipe

Other information

■ Store below 110℉(43℃)
■ May discolor certain fabrics or surfaces.